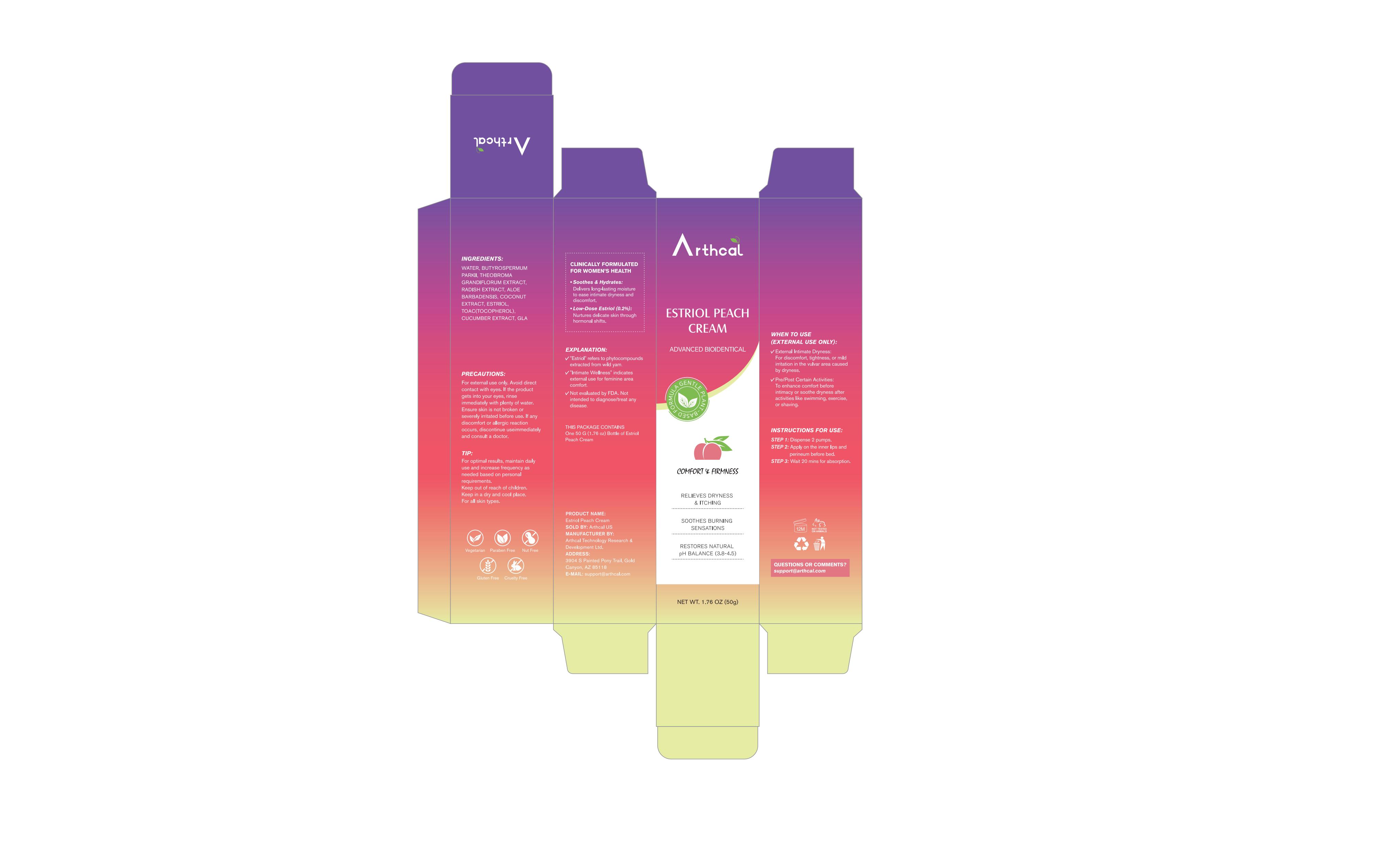 DRUG LABEL: Arthcal Bioidentical Peach Cream
NDC: 85212-0045 | Form: CREAM
Manufacturer: Beijing JUNGE Technology Co., Ltd.
Category: otc | Type: HUMAN OTC DRUG LABEL
Date: 20250816

ACTIVE INGREDIENTS: .ETA.-TOCOPHEROL 1 g/100 mL; BUTYROSPERMUM PARKII (SHEA) OIL 1 g/100 mL
INACTIVE INGREDIENTS: CUCUMBER 1 mL/100 mL; COCONUT 1 mL/100 mL; AVOCADO FRUIT WATER 86 mL/100 mL; GLUCONOLACTONE 1 mL/100 mL; THEOBROMA GRANDIFLORUM FRUIT 5 mL/100 mL; RADISH 2 mL/100 mL; ALOE BARBADENSIS LEAF 2 mL/100 mL

INDICATIONS AND USAGE

STEP 1: Dispense 2 pumps
STEP 2: Apply on the inner lips and perineum before bed
STEP 3: Wait 20 mins for absorption

DOSAGE AND ADMINISTRATION

50G/1.76OZ

PRECAUTIONS

For external use only. Avoid direct contact with eyes. If the product gets into your eyes, rinse immediately with plenty of water. Ensure skin is not broken or severely irritated before use. If any discomfort or allergic reaction occurs, discontinue useimmediately and consult a doctor. TIP: For optimal results, maintain daily use and increase frequency as needed based on personal requirements. Keep out of reach of children. Keep in a dry and cool place. For all skin types

INSTRUCTIONS FOR USE

✔️External Intimate Dryness: For discomfort, tightness, or mild irritation in the vulvar area caused by dryness.
✔️Pre/Post Certain Activities: To enhance comfort before intimacy or soothe dryness after activities like swimming, exercise, or shaving.

ACTIVE INGREDIENT

TOAC-1%

BUTYROSPERMUM PARKII-1%

INACTIVE INGREDIENT

WATER
THEOBROMA GRANDIFLORUM EXTRACT
RADISH EXTRACT
ALOE BARBADENSIS
COCONUT EXTRACT
CUCUMBER EXTRACT

PURPOSE

Soothes & Hydrates: Delivers long-lasting moisture to ease intimate dryness and discomfort.

BOXED WARNING

For external use only, Keep out of reach of children.Avoid contact with eyes.

Keep out of reach of children. lf swallowed, get medical help or contact a Poison Control Center right
away

WARNINGS

Not evaluated by FDA. Not intended to diagnose/treat any disease